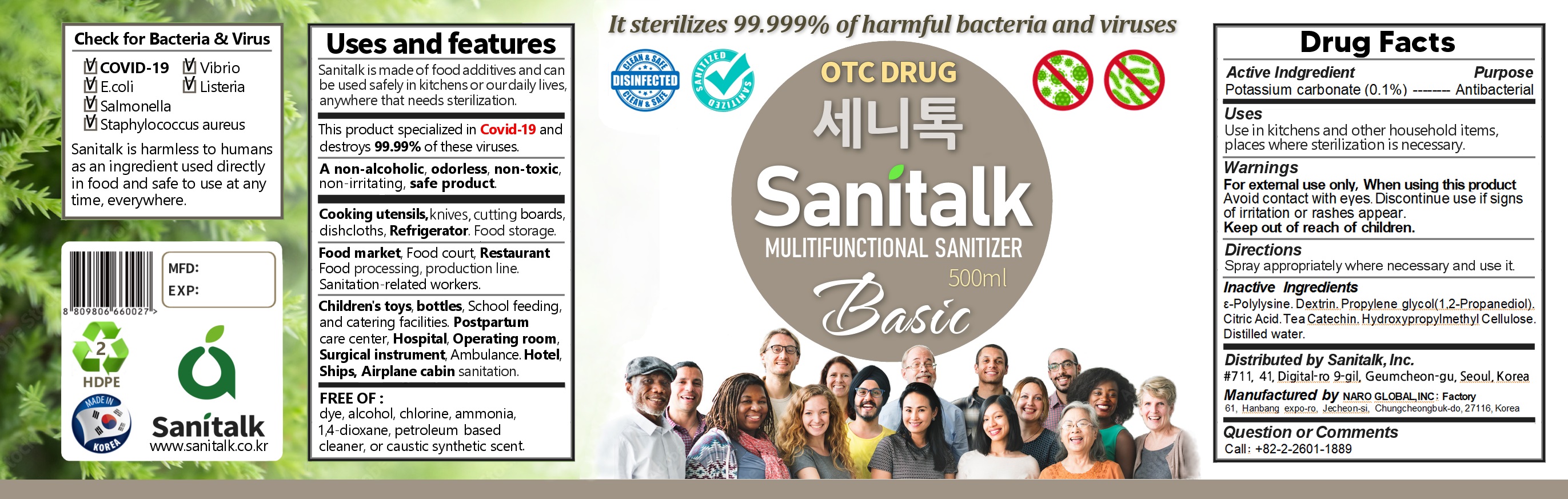 DRUG LABEL: SANITALK - SANITIZER(COVID-19)
NDC: 82486-0001 | Form: LIQUID
Manufacturer: Sanitalk Inc
Category: otc | Type: HUMAN OTC DRUG LABEL
Date: 20220114

ACTIVE INGREDIENTS: POTASSIUM CARBONATE 0.1 g/100 mL
INACTIVE INGREDIENTS: CITRIC ACID MONOHYDRATE; WATER

ACTIVE INGREDIENT

potassium carbonate

INACTIVE INGREDIENT

ε-Polylysine.Dextrin.1,2-Propanediol.Citric Acid.Tea Catechin. Hydroxypropylmethyl Cellulose.Distilled water.

PURPOSE

Sanitizer to help decrease bacteria on skin

keep out of reach of the children

INDICATIONS AND USAGE

Spray on skin as needed

WARNINGS

For external use only.

When using this product

Avoid contact with eyes. Discontinue use if signs of irritation or rashes appear.

Keep out of reach of children.

Store at room temperature.

DOSAGE AND ADMINISTRATION

for external use only